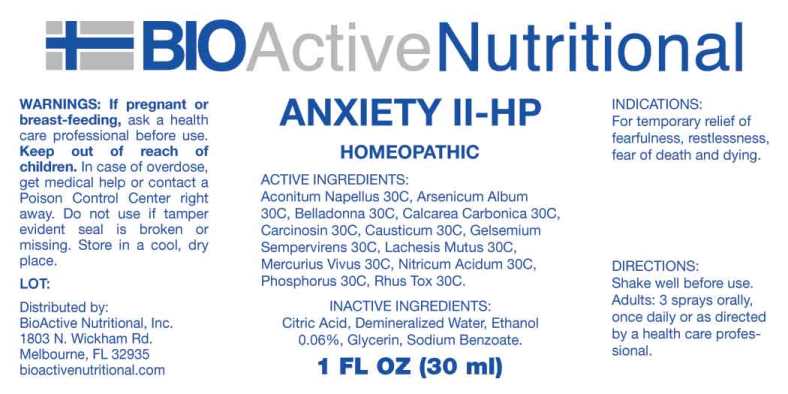 DRUG LABEL: Anxiety
NDC: 43857-0097 | Form: SPRAY
Manufacturer: BioActive Nutritional, Inc.
Category: homeopathic | Type: HUMAN OTC DRUG LABEL
Date: 20230606

ACTIVE INGREDIENTS: ACONITUM NAPELLUS WHOLE 30 [hp_C]/1 mL; ARSENIC TRIOXIDE 30 [hp_C]/1 mL; ATROPA BELLADONNA 30 [hp_C]/1 mL; OYSTER SHELL CALCIUM CARBONATE, CRUDE 30 [hp_C]/1 mL; HUMAN BREAST TUMOR CELL 30 [hp_C]/1 mL; CAUSTICUM 30 [hp_C]/1 mL; GELSEMIUM SEMPERVIRENS ROOT 30 [hp_C]/1 mL; LACHESIS MUTA VENOM 30 [hp_C]/1 mL; MERCURY 30 [hp_C]/1 mL; NITRIC ACID 30 [hp_C]/1 mL; PHOSPHORUS 30 [hp_C]/1 mL; TOXICODENDRON PUBESCENS LEAF 30 [hp_C]/1 mL
INACTIVE INGREDIENTS: WATER; GLYCERIN; SODIUM BENZOATE; CITRIC ACID MONOHYDRATE; ALCOHOL

Drug Facts:

ACTIVE INGREDIENTS:

Aconitum Napellus 30C, Arsenicum Album 30C, Belladonna 30C, Calcarea Carbonica 30C, Carcinosin 30C, Causticum 30C, Gelsemium Sempervirens 30C, Lachesis Mutus 30C, Mercurius Vivus 30C, Nitricum Acidum 30C, Phosphorus 30C, Rhus Tox 30C.

INDICATIONS:

For temporary relief of fearfulness, restlessness, fear of death and dying.

WARNINGS:

If pregnant or breast-feeding, ask a health care professional before use.

Keep out of reach of children. In case of overdose, get medical help or contact a Poison Control Center right away.

Do not use if tamper evident seal is broken or missing.

Store in cool, dry place.

Keep out of reach of children. In case of overdose, get medical help or contact a Poison Control Center right away.

DIRECTIONS:

Shake well before use.

Adults: 3 sprays orally, once daily or as directed by a health care professional.

INDICATIONS:

For temporary relief of fearfulness, restlessness, fear of death and dying.

INACTIVE INGREDIENTS:

Citric Acid, Demineralized Water, Ethanol 0.06%, Glycerin, Sodium Benzoate.

QUESTIONS:

Distributed by:

BioActive Nutritional, Inc.

1803 N. Wickham Rd.

Melbourne, FL 32935

bioactivenutritional.com

PACKAGE LABEL DISPLAY:

BIOActive Nutritional

ANXIETY II-HP

HOMEOPATHIC

1 FL OZ (30 ml)